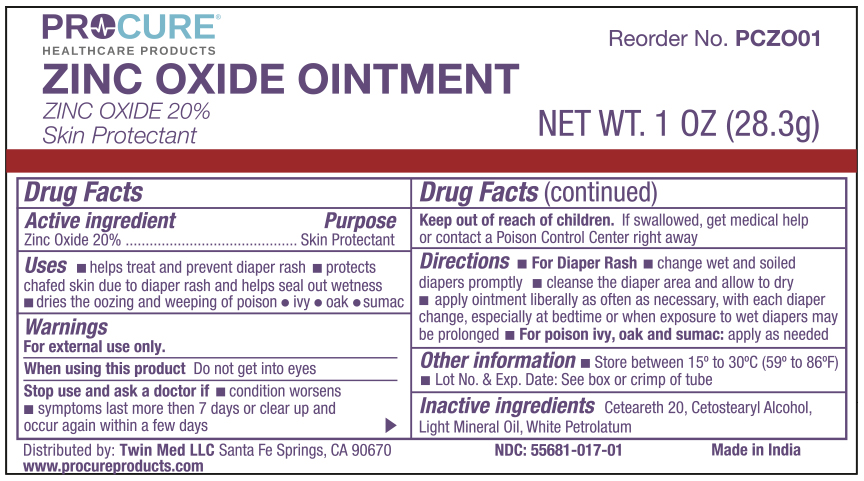 DRUG LABEL: ProCure Zinc Oxide
NDC: 55681-017 | Form: OINTMENT
Manufacturer: Twin Med LLC
Category: otc | Type: HUMAN OTC DRUG LABEL
Date: 20250615

ACTIVE INGREDIENTS: ZINC OXIDE 20 g/100 g
INACTIVE INGREDIENTS: LIGHT MINERAL OIL; WHITE PETROLATUM; CETOSTEARYL ALCOHOL; CETEARETH-20

Active Ingredient

Zinc Oxide

Purpose

Skin Protectant

Uses

- helps treat and prevent diaper rash
- protects chafed skin due to diaper rash and helps seal out wetness
- dries the ozzing and weeping of poison ivy, poison oak and posion sumac

Warnings

For external use only.

When using this product do not get into eyes

Stop use and ask a doctor if

- condition worsens
- symptoms last more than 7 days or clear up and occur again within a few days

Keep out of reach of children. If swallowed, get medical help or contact a Poison Control Center right away

Directions

For Diaper Rash:

- change wet and soiled diapers promptly
- cleanse the siaper area and allow to dry
- apply ointment liberally as often as necessary, with each diaper change, especially at bedtime or when exposure to wet diapers may be prolonged

For poison ivy, oak and suman: apply as needed

Inactive ingredients

Inactive ingredients: Ceteareth 20, Cetostearyl Alcohol, Light Mineral Oil, Petrolatum